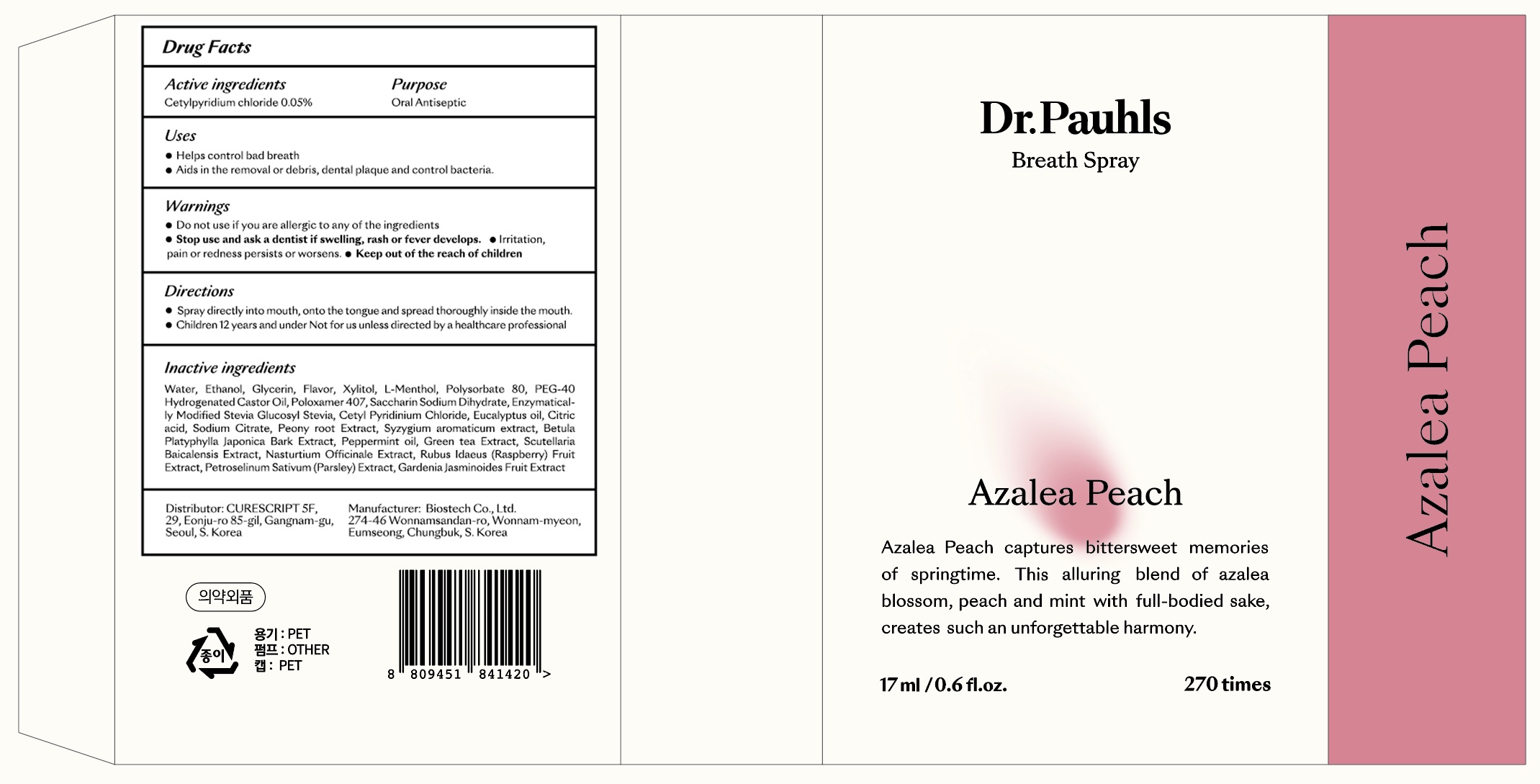 DRUG LABEL: Breath mellow Azalea Peach
NDC: 72265-101 | Form: SPRAY
Manufacturer: CURESCRIPT
Category: otc | Type: HUMAN OTC DRUG LABEL
Date: 20210223

ACTIVE INGREDIENTS: CETYLPYRIDINIUM CHLORIDE 0.0085 g/17 mL
INACTIVE INGREDIENTS: Water; Alcohol; Glycerin

ACTIVE INGREDIENT

CETYLPYRIDINIUM CHLORIDE 0.05%

INACTIVE INGREDIENTS

Water, Ethanol, Glycerin , Flavor , Xylitol , L-Menthol, Polysorbate 80 , PEG-40 Hydrogenated Castor Oil , Poloxamer 407 , Saccharin Sodium Dihydrate , Enzymatically Modified Stevia Glucosyl Stevia , Cetyl Pyridinium Chloride , Eucalyptus oil , Citric acid, Sodium Citrate, Peony root Extract, Syzygium aromaticum extract , Betula Platyphylla Japonica Bark Extract , Peppermint oil , Green tea Extract , Scutellaria Baicalensis Extract , Nasturtium Officinale Extract , Rubus Idaeus (Raspberry) Fruit Extract , Petroselinum Sativum (Parsley) Extract, Gardenia Jasminoides Fruit Extract

PURPOSE

Oral Antiseptic

WARNINGS

■ Do not use if you are allergic to any of the ingredients

Stop use and ask a dentist if ■Swelling, rash or fever develops. ■ Irritation, pain or redness persists or worsens.

Keep out of the reach of children

KEEP OUT OF REACH OF CHILDREN

Uses

■ Helps control bad breath
■ aids in the removal or debris, dental plaque and control bacteria.

Directions

■ Spray directly into mouth, onto the tongue and spread thoroughly inside the mouth.
■ Children 12 years and under Not for us unless directed by a healthcare professional